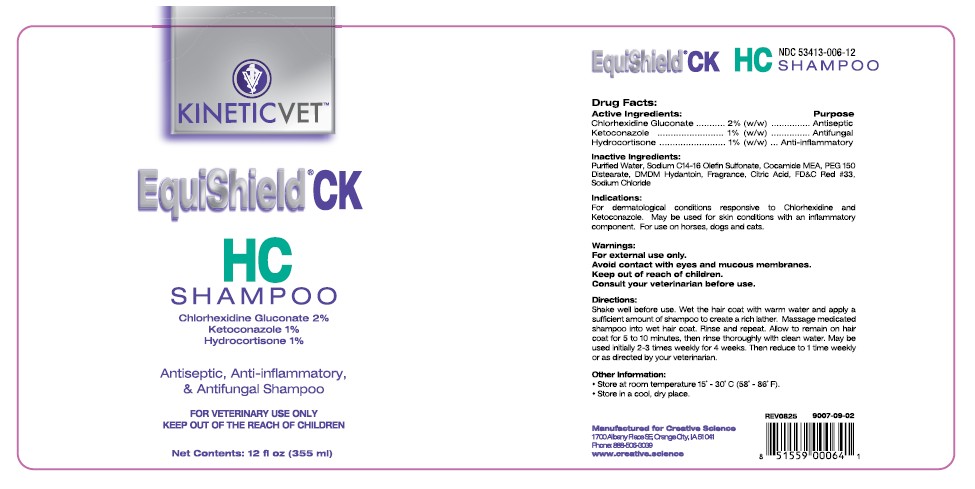 DRUG LABEL: EquiShield CK HC
NDC: 53413-006 | Form: SHAMPOO
Manufacturer: Creative Science
Category: animal | Type: OTC ANIMAL DRUG LABEL
Date: 20251206

ACTIVE INGREDIENTS: CHLORHEXIDINE GLUCONATE 20 mg/1 mL; KETOCONAZOLE 10 mg/1 mL; HYDROCORTISONE 10 mg/1 mL

EquiShield CK HC SHAMPOO

NDC 53413-006-12 Drug Facts: Purpose

Active Ingredients:

Chlorhexidine Gluconate ........... 2% (w/w)......................Antiseptic
Ketoconazole ........................... 1% (w/w).....................Antifungal
Hydrocortisone ........................ 1% (w/w)...........Anti-inflammatory

Inactive Ingredients:

Purified Water, Sodium C14-16 Olefin Sulfonate, Cocamide MEA, PEG 150 Distearate, DMDM Hydantoin, Fragrance, Citric Acid, FD&C Red #33, Sodium Chloride

Indications:

For dermatological conditions responsive to Chlorhexidine and Ketoconazole. May be used for skin conditions with an inflammatory component. For use on horses, dogs and cats.

Warnings:

For external use only.
Avoid contact with eyes and mucous membranes.
Keep out of reach of children.
Consult your veterinarian before use.

Directions:

Shake well before use. Wet the hair coat with warm water and apply a sufficient amount of shampoo to create a rich lather. Massage medicated shampoo into wet hair coat. Rinse and repeat. Allow to remain on hair coat for 5 to 10 minutes, then rinse thoroughly with clean water. May be used initially 2-3 times weekly for 4 weeks. Then reduce to 1 time weekly or as directed by your veterinarian.

Other Information:

• Store at room temperature 15˚ - 30˚C (58˚ - 86˚F).
• Store in a cool, dry place.

Rev 0825 9007-09-02
UPC 851559000641
Manufactured for Creative Science
1700 Albany Place SE, Orange City, IA 51041Phone 888-506-3039
www.creative.science

KINETIC™VET

EquiShield CK HC SHAMPOO

Chlorhexidine Gluconate 2%

Ketoconazole 1%

Hydrocortisone 1%

Antiseptic & Anti-inflammatory & Antifungal Shampoo

FOR VETERINARY USE ONLY

KEEP OUT OF THE REACH OF CHILDREN

Net Contents: 12 fl oz (355ml)